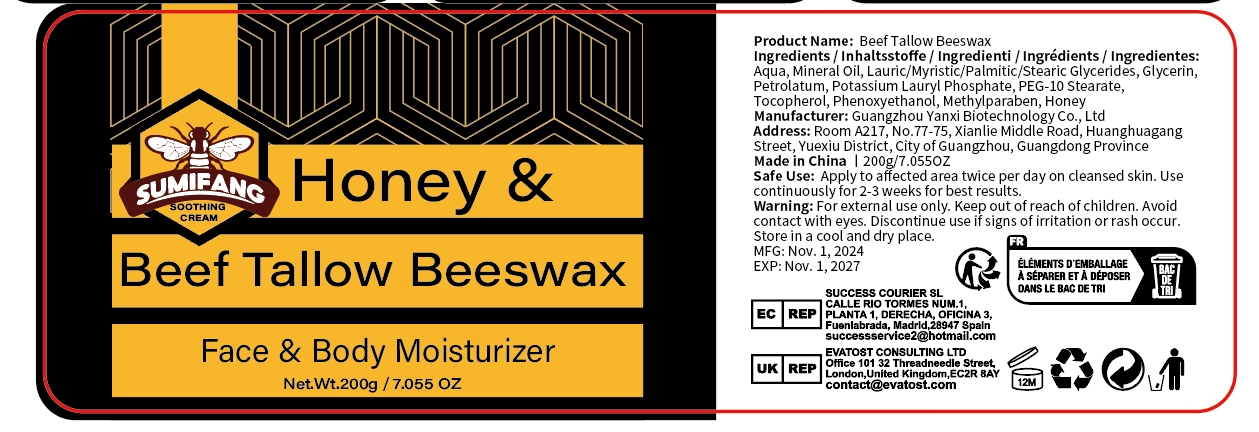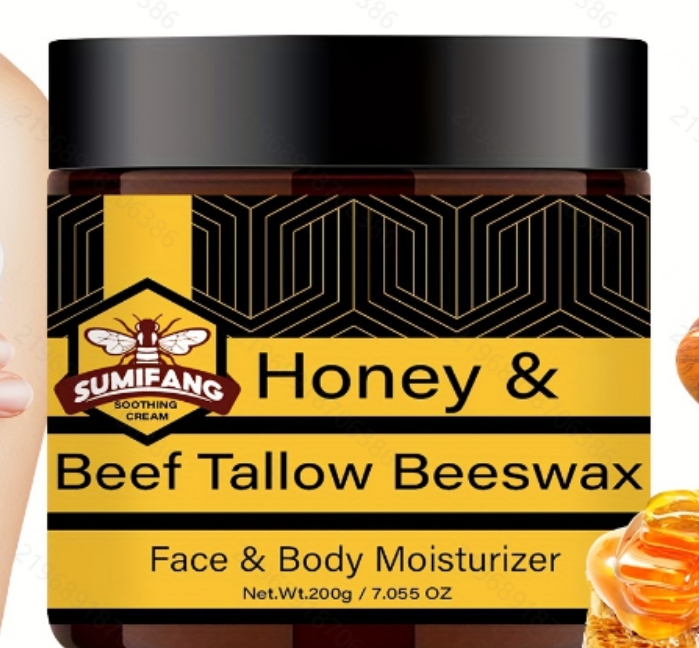 DRUG LABEL: Beef Tallow Beeswax
NDC: 84025-258 | Form: CREAM
Manufacturer: Guangzhou Yanxi Biotechnology Co., Ltd
Category: otc | Type: HUMAN OTC DRUG LABEL
Date: 20241110

ACTIVE INGREDIENTS: MINERAL OIL 5 mg/100 g; GLYCERIN 3 mg/100 g
INACTIVE INGREDIENTS: WATER

DOSAGE AND ADMINISTRATION

Apply to affected area twice per day on cleansed skin. Use continuouslyfor2-3 weeks for best results.

WARNINGS

keep out of children

INACTIVE INGREDIENT

for daily face and body care.

INDICATIONS AND USAGE

for daily face and body care

keep out of children

PURPOSE

Moisturize the face and body